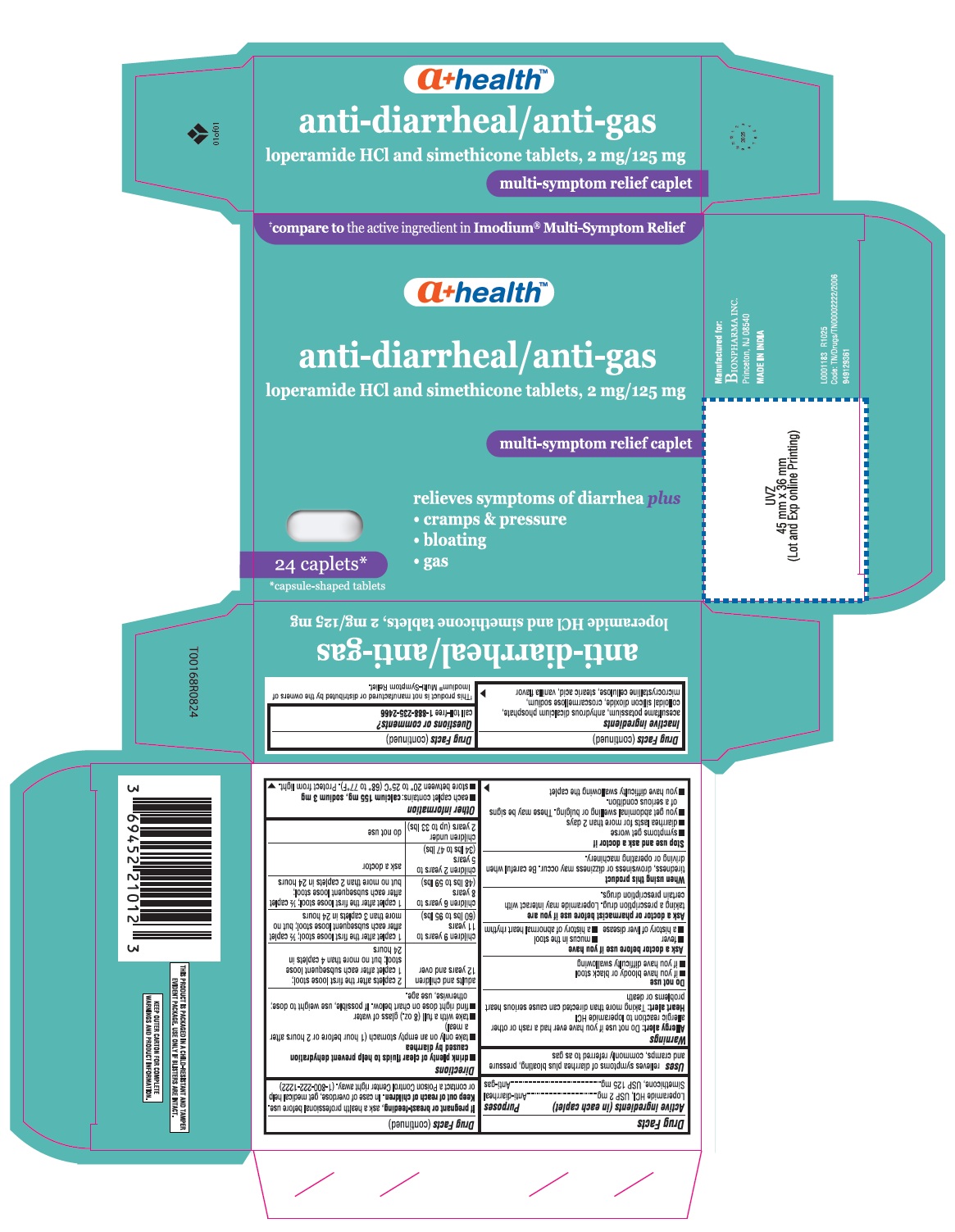 DRUG LABEL: Loperamide hydrochloride and Simethicone
NDC: 69452-531 | Form: TABLET
Manufacturer: Bionpharma Inc.
Category: otc | Type: HUMAN OTC DRUG LABEL
Date: 20260105

ACTIVE INGREDIENTS: LOPERAMIDE HYDROCHLORIDE 2 mg/1 1; DIMETHICONE 125 mg/1 1
INACTIVE INGREDIENTS: ACESULFAME POTASSIUM; CALCIUM PHOSPHATE, DIBASIC, ANHYDROUS; SILICON DIOXIDE; CROSCARMELLOSE SODIUM; CELLULOSE, MICROCRYSTALLINE; STEARIC ACID; VANILLA

Bion Loperamide Simethicone Tablets

Drug Facts

Active ingredients (in each caplet)

Loperamide HCl, USP 2 mg
Simethicone, USP 125 mg

Purposes

Anti-diarrheal

Anti-gas

Uses

relieves symptoms of diarrhea plus bloating, pressure and cramps, commonly referred to as gas

Warnings

Allergy alert

Do not use if you have ever had a rash or other allergic reaction to loperamide HCl

Heart alert

Taking more than directed can cause serious heart problems or death

Do not use

- if you have bloody or black stool
- if you have difficulty swallowing

Ask a doctor before use if you have

- fever
- mucus in the stool
- a history of liver disease
- a history of abnormal heart rhythm

Ask a doctor or pharmacist before use if you aretaking a prescription drug. Loperamide may interact with certain prescription drugs.

WHEN USING

When using this producttiredness, drowsiness or dizziness may occur. Be careful when driving or operating machinery.

Stop use and ask a doctor if

- symptoms get worse
- diarrhea lasts for more than 2 days
- you get abdominal swelling or bulging. These may be signs of a serious condition.
- you have difficulty swallowing the caplet

PREGNANCY OR BREAST FEEDING

If pregnant or breast-feeding,ask a health professional before use.

Keep out of reach of children.In case of overdose, get medical help or contact a Poison Control Center right away. (1-800-222-1222)

Directions

- drink plenty of clear fluids to help prevent dehydration caused by diarrhea
- take only on an empty stomach (1 hour before or 2 hours after a meal)
- take with a full (8 oz.) glass of water
- find right dose on chart below. If possible, use weight to dose; otherwise, use age.

adults and children 12 years and over | 2 caplets after the first loose stool; 1 caplet after each subsequent loose stool; but no more than 4 caplets in 24 hours
children 9 years to 11 years (60 lbs to 95 lbs) | 1 caplet after the first loose stool; ½ caplet after each subsequent loose stool; but no more than 3 caplets in 24 hours
children 6 years to 8 years (48 lbs to 59 lbs) | 1 caplet after the first loose stool; ½ caplet after each subsequent loose stool; but no more than 2 caplets in 24 hours
children 2 years to 5 years (34 lbsto 47 lbs) | ask a doctor
children under 2 years (up to 33 lbs) | do not use

Other information

- each caplet contains: calcium 155 mg, sodium 3 mg
- store between 20° to 25°C (68° to 77°F). Protect from light.

Inactive ingredients

acesulfame potassium, anhydrous dicalcium phosphate, colloidal silicon dioxide, croscarmellose sodium, microcrystalline cellulose, stearic acid, vanilla flavor

Questions or comments?

call toll-free 1-888-235-2466

ⱡThis product is not manufactured or distributed by the owners of Imodium®Multi-Symptom Relief

THIS PRODUCT IS PACKAGED IN A CHILD-RESISTANT AND TAMPEREVIDENT PACKAGE. USE ONLY IF BLISTERS ARE INTACT.

KEEP OUTER CARTON FOR COMPLETE WARNINGS AND PRODUCT INFORMATION.

Manufactured for:

BIONPHARMA

Princeton, NJ 08540

MADE IN INDIA

L0001183

R1025

Code: TN/Drugs/TN00002222/2006

949129361

PRINCIPAL DISPLAY PANEL

ⱡCompare to the active ingredients in Imodium®Multi-Symptom Relief

anti-diarrheal/anti-gas

Loperamide HCl and simethicone tablets, 2 mg/125 mg

multi-symptom relief caplet

Relieves symptoms of diarrhea plus

- Cramps & Pressure
- Bloating
- Gas

24 Caplets*

*Capsule-shaped Tablets